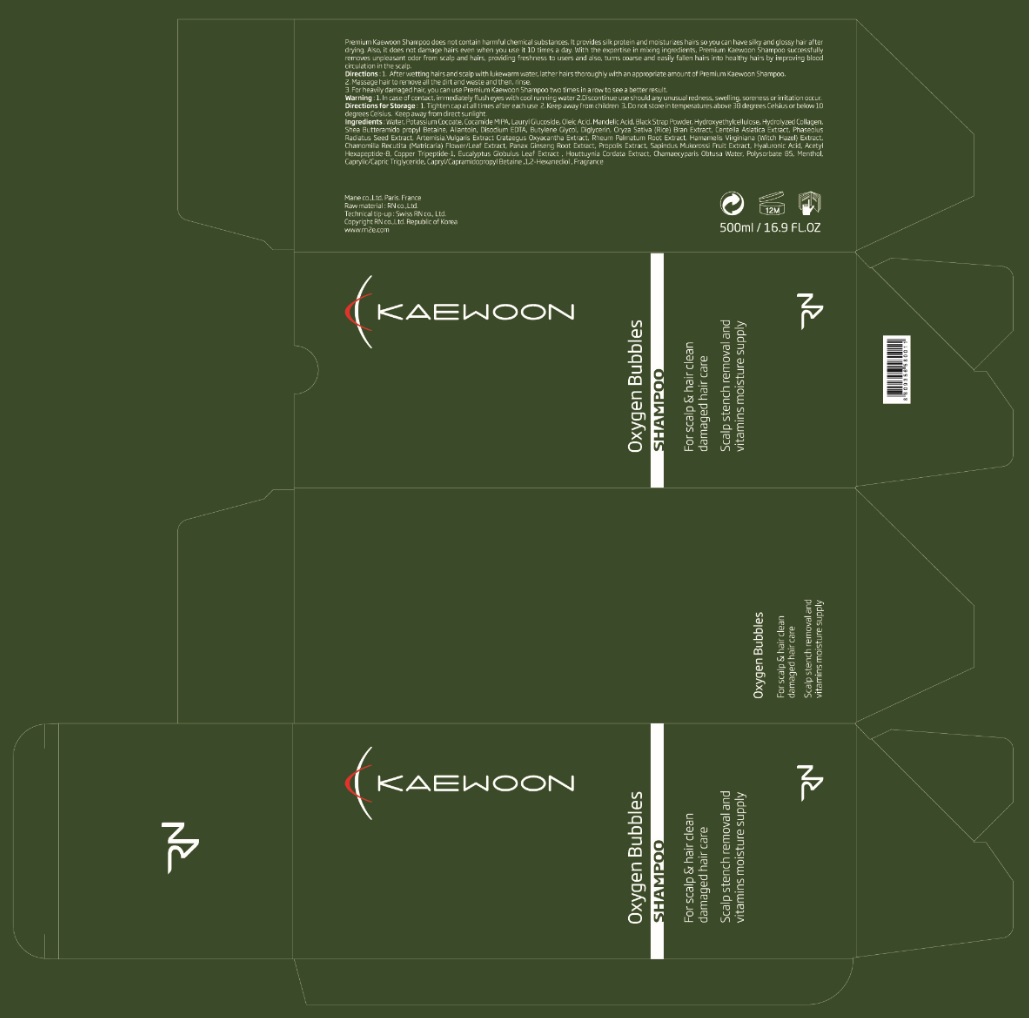 DRUG LABEL: KAEWOON
NDC: 71237-002 | Form: SHAMPOO
Manufacturer: RNCARE
Category: otc | Type: HUMAN OTC DRUG LABEL
Date: 20211004

ACTIVE INGREDIENTS: MENTHOL, UNSPECIFIED FORM 1 mg/1 mL
INACTIVE INGREDIENTS: WATER; POTASSIUM COCOATE; COCO MONOISOPROPANOLAMIDE; LAURYL GLUCOSIDE; OLEIC ACID; MANDELIC ACID; SPANISH SARDINE; HYDROXYETHYL CELLULOSE (100 MPA.S AT 2%); ALLANTOIN; EDETATE DISODIUM ANHYDROUS; BUTYLENE GLYCOL; DIGLYCERIN; RICE BRAN; CENTELLA ASIATICA; MUNG BEAN; ARTEMISIA VULGARIS ROOT; RHEUM PALMATUM ROOT; HAMAMELIS VIRGINIANA TOP; MATRICARIA CHAMOMILLA FLOWERING TOP; ASIAN GINSENG; PROPOLIS WAX; SAPINDUS MUKOROSSI FRUIT; ACETYL HEXAPEPTIDE-8; PREZATIDE COPPER; EUCALYPTUS GLOBULUS LEAF; HOUTTUYNIA CORDATA FLOWERING TOP; CHAMAECYPARIS OBTUSA WOOD OIL; POLYSORBATE 85; MEDIUM-CHAIN TRIGLYCERIDES; CAPRYL/CAPRAMIDOPROPYL BETAINE; 1,2-HEXANEDIOL

71237-002_V3

ACTIVE INGREDIENT

Menthol 0.1%

PURPOSE

Hair Care

INDICATIONS AND USAGE

Damaged hair care

DOSAGE AND ADMINISTRATION

1. After wetting hairs and scalp with lukewarm water, lather hairs thoroughly with an appropriate amount of premium Kaewoon Shampoo.

2. Massage hair to removed all the dirt and waste and then, rinse.

3. For heavily damaged hair, you can use Premium Kaewoon Shampoo two times in a row to see a better result.

WARNINGS

In case of eye contact, immediately rinse with water

Stop use if unusual redness, swelling, soreness or irritation occur

Keep out of reach of children